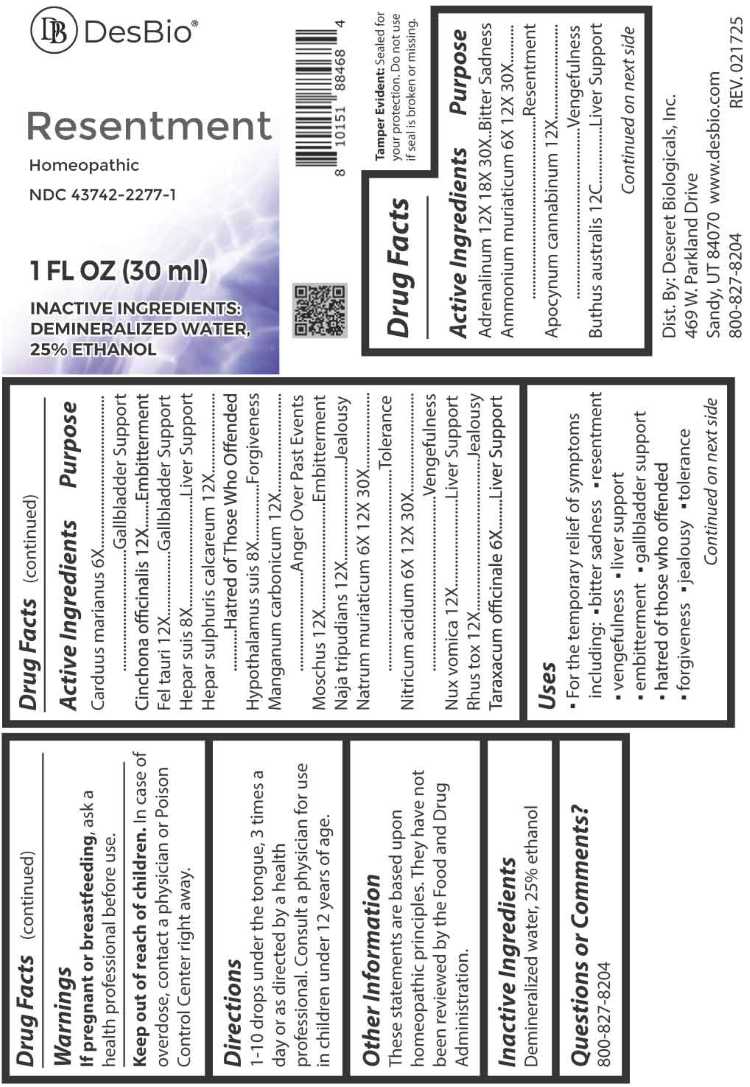 DRUG LABEL: Resentment
NDC: 43742-2277 | Form: LIQUID
Manufacturer: Deseret Biologicals, Inc.
Category: homeopathic | Type: HUMAN OTC DRUG LABEL
Date: 20260226

ACTIVE INGREDIENTS: EPINEPHRINE 12 [hp_X]/1 mL; AMMONIUM CHLORIDE 6 [hp_X]/1 mL; APOCYNUM CANNABINUM ROOT 12 [hp_X]/1 mL; ANDROCTONUS AUSTRALIS VENOM 12 [hp_C]/1 mL; MILK THISTLE 6 [hp_X]/1 mL; CINCHONA OFFICINALIS BARK 12 [hp_X]/1 mL; BOS TAURUS BILE 12 [hp_X]/1 mL; PORK LIVER 8 [hp_X]/1 mL; CALCIUM SULFIDE 12 [hp_X]/1 mL; SUS SCROFA HYPOTHALAMUS 8 [hp_X]/1 mL; MANGANESE CARBONATE 12 [hp_X]/1 mL; MOSCHUS MOSCHIFERUS MUSK SAC RESIN 12 [hp_X]/1 mL; NAJA NAJA VENOM 12 [hp_X]/1 mL; SODIUM CHLORIDE 6 [hp_X]/1 mL; NITRIC ACID 6 [hp_X]/1 mL; STRYCHNOS NUX-VOMICA SEED 12 [hp_X]/1 mL; TOXICODENDRON PUBESCENS LEAF 12 [hp_X]/1 mL; TARAXACUM OFFICINALE 6 [hp_X]/1 mL
INACTIVE INGREDIENTS: WATER; ALCOHOL

DRUG FACTS:

ACTIVE INGREDIENT:

Adrenalinum 12X, 18X, 30X, Ammonium Muriaticum 6X, 12X, 30X, Apocynum Cannabinum 12X, Buthus Australis 12C, Carduus Marianus 6X, Cinchona Officinalis 12X, Fel Tauri 12X, Hepar Suis 8X, Hepar Sulphuris Calcareum 12X, Hypothalamus Suis 8X, Manganum Carbonicum 12X, Moschus 12X, Naja Tripudians 12X, Natrum Muriaticum 6X, 12X, 30X, Nitricum Acidum 6X, 12X, 30X, Nux Vomica 12X, Rhus Tox 12X, Taraxacum Officinale 6X

PURPOSE:

Adrenalinum – Bitter Sadness, Ammonium Muriaticum - Resentment, Apocynum Cannabinum - Vengefulness, Buthus Australis – Liver Support, Carduus Marianus – Gallbladder Support, Cinchona Officinalis - Embitterment, Fel Tauri – Gallbladder Support, Hepar Suis – Liver Support, Hepar Sulphuris Calcareum – Hatred of Those Who Offended, Hypothalamus Suis - Forgiveness, Manganum Carbonicum – Anger Over Past Events, Moschus - Embitterment, Naja Tripudians - Jealousy, Natrum Muriaticum - Tolerance, Nitricum Acidum - Vengefulness, Nux Vomica – Liver Support, Rhus Tox - Jealousy, Taraxacum Officinale – Liver Support

USES:

• For the temporary relief of symptoms including:

• bitter sadness • resentment • vengefulness • liver support • embitterment • gallbladder support

• hatred of those who offended • forgiveness • jealousy • tolerance

These statements are based upon homeopathic principles. They have not been reviewed by the Food and Drug Administration.

WARNINGS:

If pregnant or breastfeeding, ask a health professional before use.

Keep out of reach of children. In case of overdose, contact a physician or Poison Control Center right away.

Tamper Evident: Sealed for your protection. Do not use if seal is broken or missing.

KEEP OUT OF REACH OF CHILDREN:

In case of overdose, contact a physician or Poison Control Center right away.

DIRECTIONS:

1-10 drops under the tongue, 3 times a day or as directed by a health professional. Consult a physician for use in children under 12 years of age.

INACTIVE INGREDIENTS:

Demineralized water, 25% ethanol

QUESTIONS:

Dist. By: Deseret Biologicals, Inc.

469 W. Parkland Drive

Sandy, UT 84070

www.desbio.com

800-827-8204

PACKAGE LABEL DISPLAY:

DesBio

Resentment

Homeopathic

NDC 43742-2277-1

1 FL OZ (30ml)